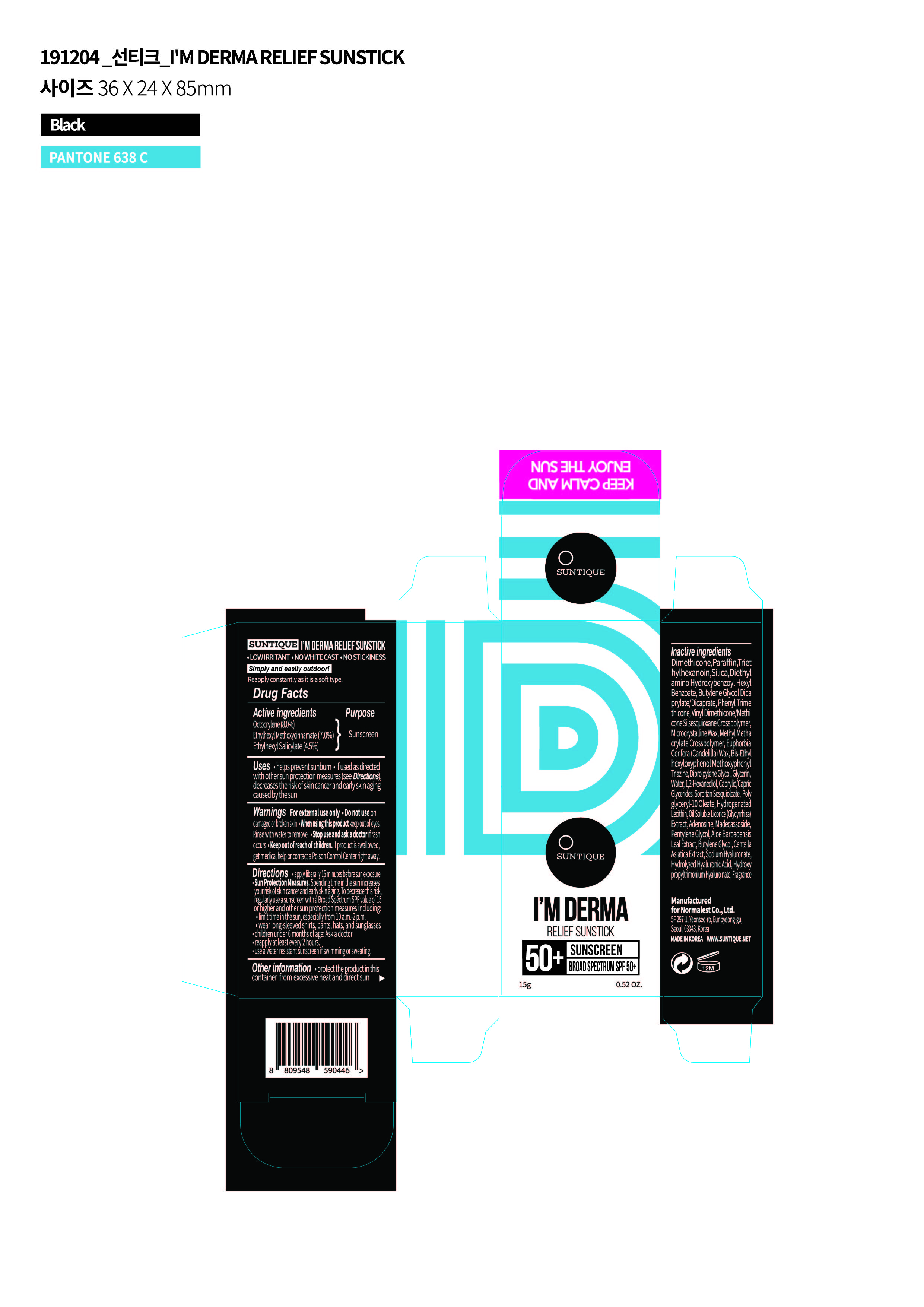 DRUG LABEL: IM DERMA RELIEF SUNSTICK
NDC: 72284-0010 | Form: STICK
Manufacturer: Normalest Co., Ltd.
Category: otc | Type: HUMAN OTC DRUG LABEL
Date: 20191205

ACTIVE INGREDIENTS: OCTINOXATE 1.05 g/15 g; OCTOCRYLENE 1.2 g/15 g; OCTISALATE 0.675 g/15 g
INACTIVE INGREDIENTS: HYALURONIC ACID; CENTELLA ASIATICA; DIMETHICONE; PARAFFIN; TRIETHYLHEXANOIN; SILICON DIOXIDE; DIETHYLAMINO HYDROXYBENZOYL HEXYL BENZOATE; PHENYL TRIMETHICONE; BUTYLENE GLYCOL DICAPRYLATE/DICAPRATE; VINYL DIMETHICONE/METHICONE SILSESQUIOXANE CROSSPOLYMER; MICROCRYSTALLINE WAX; CANDELILLA WAX; METHYL METHACRYLATE/GLYCOL DIMETHACRYLATE CROSSPOLYMER; BEMOTRIZINOL; DIPROPYLENE GLYCOL; GLYCERIN; WATER; 1,2-HEXANEDIOL; SORBITAN SESQUIOLEATE; HYDROGENATED SOYBEAN LECITHIN; POLYGLYCERYL-10 OLEATE; GLYCYRRHIZA GLABRA; ADENOSINE; MADECASSOSIDE; PENTYLENE GLYCOL; BUTYLENE GLYCOL; ALOE VERA LEAF; HYALURONATE SODIUM

SUNTIQUE I'M DERMA RELIEF SUNSTICK